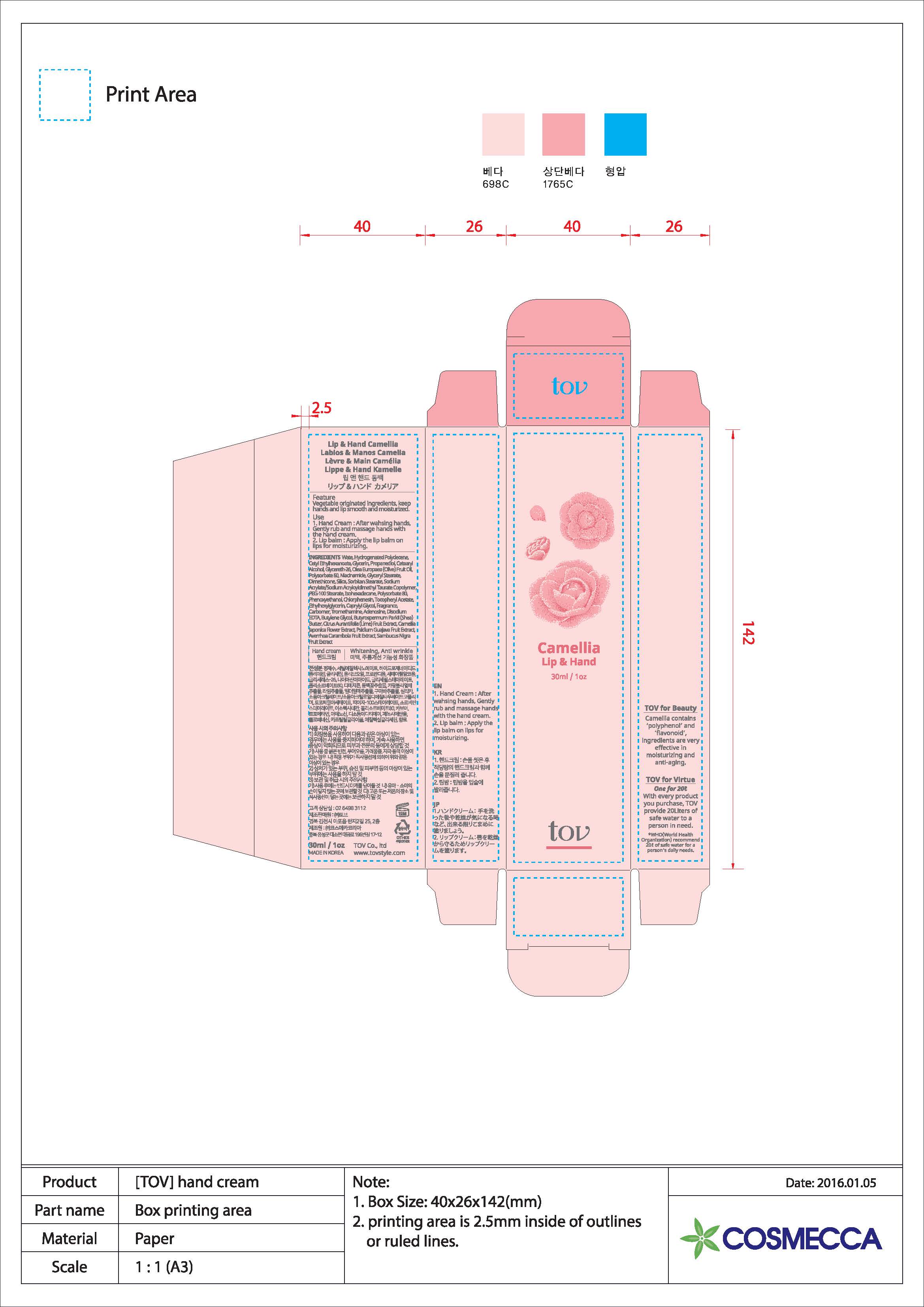 DRUG LABEL: Lip And Hand Camellia
NDC: 71077-0005 | Form: CREAM
Manufacturer: TOV Co., ltd
Category: otc | Type: HUMAN OTC DRUG LABEL
Date: 20161108

ACTIVE INGREDIENTS: NIACINAMIDE 2 g/100 mL; ADENOSINE 0.04 g/100 mL
INACTIVE INGREDIENTS: GLYCERIN; BUTYLENE GLYCOL

Drug Facts

ACTIVE INGREDIENT

Niacinamide, Adenosine

INACTIVE INGREDIENT

Glycerin, Butylene Glycol, Etc.

PURPOSE

Hand Cream, Whitening, Anti Wrinkle

INDICATIONS AND USAGE

1. Hand Cream : After Washing hands, Gently rub and massage hands with the hand cream.
2. Lip Balm : Apply the lip balm on lips for moisturizing.

DOSAGE AND ADMINISTRATION

for external use only

WARNINGS

1. Do not use in the following cases(Eczema and scalp wounds)
2.Side Effects
1)Due to the use of this druf if rash, irritation, itching and symptopms of hypersnesitivity occur dicontinue use and consult your phamacisr or doctor
3.General Precautions
1)If in contact with the eyes, wash out thoroughty with water If the symptoms are servere, seek medical advice immediately
2)This product is for exeternal use only. Do not use for internal use
4.Storage and handling precautions
1)If possible, avoid direct sunlight and store in cool and area of low humidity
2)In order to maintain the quality of the product and avoid misuse
3)Avoid placing the product near fire and store out in reach of children

keep out of reach of the children